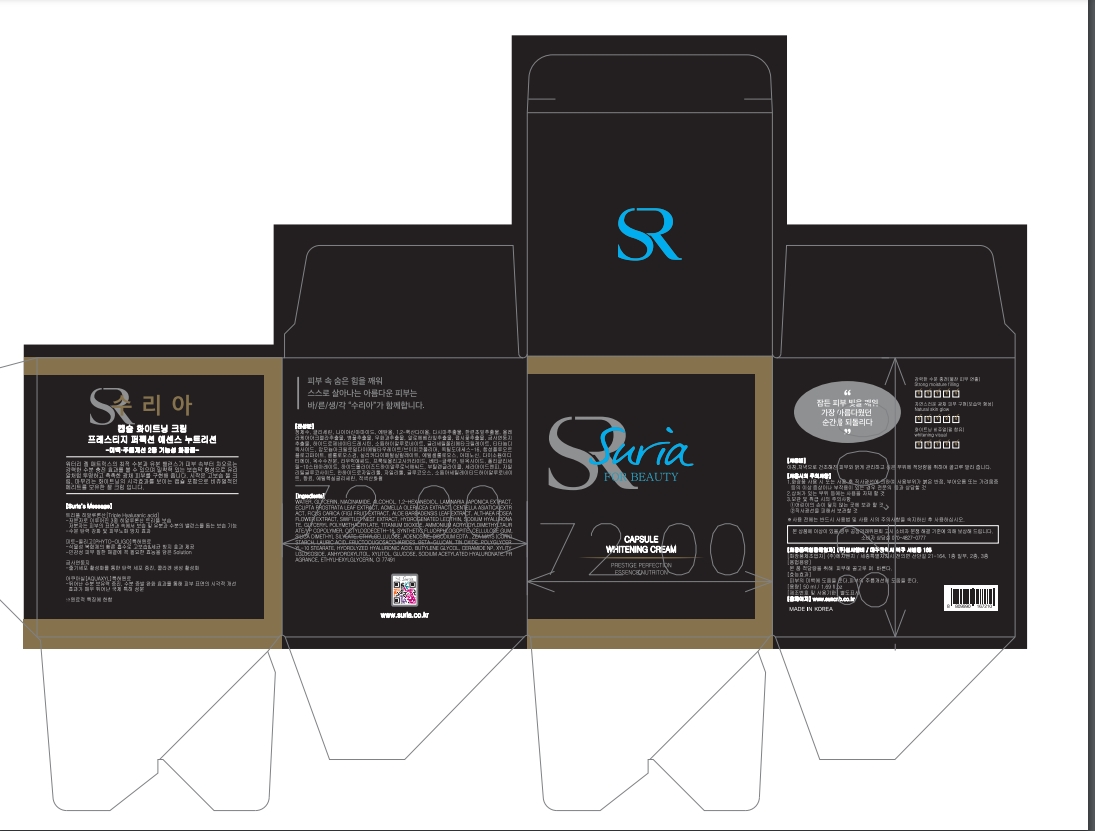 DRUG LABEL: SURIA WHITENING
NDC: 81479-005 | Form: CREAM
Manufacturer: SUN C&B
Category: otc | Type: HUMAN OTC DRUG LABEL
Date: 20210131

ACTIVE INGREDIENTS: NIACINAMIDE 2 g/50 mL; GLYCERIN 2 g/50 mL
INACTIVE INGREDIENTS: WATER 46 g/50 mL

ACTIVE INGREDIENT

Glycerin, Niacinamide

INACTIVE INGREDIENT

Water, etc

PURPOSE

Skin Protectant - Anti-Wrinkle, Whitening

Keep out of reach of the children

INDICATIONS AND USAGE

Apply a small amount of cream on the face and gently pat the skin.

DOSAGE AND ADMINISTRATION

For external use only

WARNINGS

1. If any of the following Symptoms occur, Cease use immediately. Continued usage would exacerbate the
symptoms. If symptoms persist, consult a doctor.
1) During of after usage, if red spots appear or you suffer from welling or itching or any other abnormal
symptoms after direct exposure to sunlight, consult a doctor immediately.
2)Avoid usage on cuts and wounds.
3) Storage and usage precautions.
A) Keep it out of reach of children.
B) Avoid exposure to direct sunlight during storage.